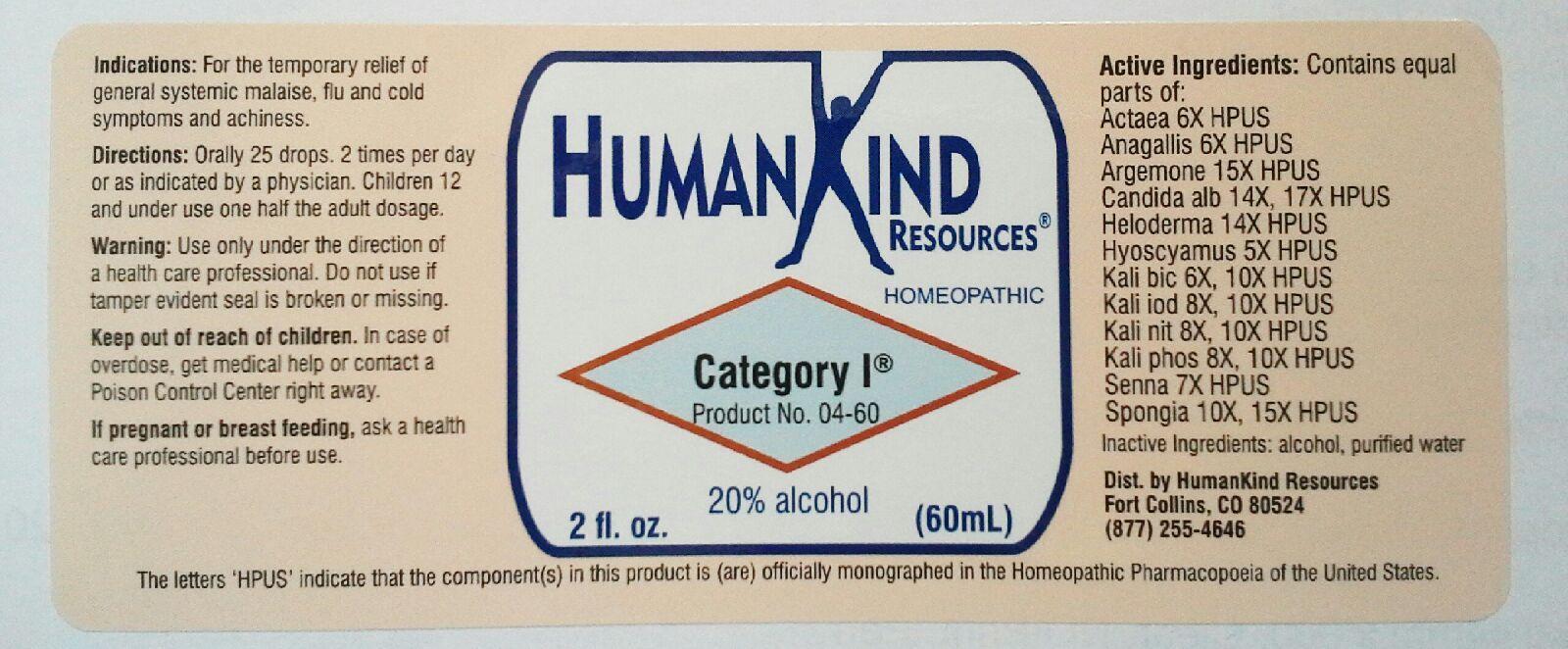 DRUG LABEL: Category I
NDC: 64616-082 | Form: LIQUID
Manufacturer: Vitality Works, Inc
Category: homeopathic | Type: HUMAN OTC DRUG LABEL
Date: 20251217

ACTIVE INGREDIENTS: ACTAEA SPICATA ROOT 6 [hp_X]/1 mL; ANAGALLIS ARVENSIS 6 [hp_X]/1 mL; ARGEMONE MEXICANA 15 [hp_X]/1 mL; CANDIDA ALBICANS 17 [hp_X]/1 mL; HELODERMA HORRIDUM VENOM 14 [hp_X]/1 mL; HYOSCYAMUS NIGER 5 [hp_X]/1 mL; POTASSIUM DICHROMATE 10 [hp_X]/1 mL; POTASSIUM IODIDE 10 [hp_X]/1 mL; POTASSIUM NITRATE 10 [hp_X]/1 mL; POTASSIUM PHOSPHATE, DIBASIC 10 [hp_X]/1 mL; SENNA LEAF 7 [hp_X]/1 mL; SPONGIA OFFICINALIS SKELETON, ROASTED 15 [hp_X]/1 mL
INACTIVE INGREDIENTS: ALCOHOL; WATER

Category I

Category I

Actaea Spicata 6X Kali Bichromicum 6X, 10X

Anagallis Arvensis 6X Kali Iodatum 8X, 10X

Argemone Mexicana 15X Kali Nitricum 8X, 10X

Candida Albicans 14X, 17X Kali Phosphoricum 8X, 10X

Heloderma 14X Senna 7X

Hyoscyamus Niger 5X Spongia Tosta 10X, 15X

Category I

Alcohol, Purified Water,

Category I

Use only under the direction of a health care professional. Do not use if tamper evident seal is broken or missing.

Category I

Keep out of reach of children. In case of overdose, get medical help or contact aPoison Control Center right away.

Category I

For the temporary relief of general systemic malise, flu and cold symptoms and achiness.

Category I

Orally 25 drops, 2 times per day or as indicated by a physician. Children 12 and under use one half the adult.

Category I

Temporarily eases malaise, flu and cold symptoms and aches.